DRUG LABEL: Unknown
Manufacturer: Food and Drug Administration
Category: other | Type: Indexing - Pharmacologic Class
Date: 20140423

ZIPRASIDONE Pharmacologic Class Indexing